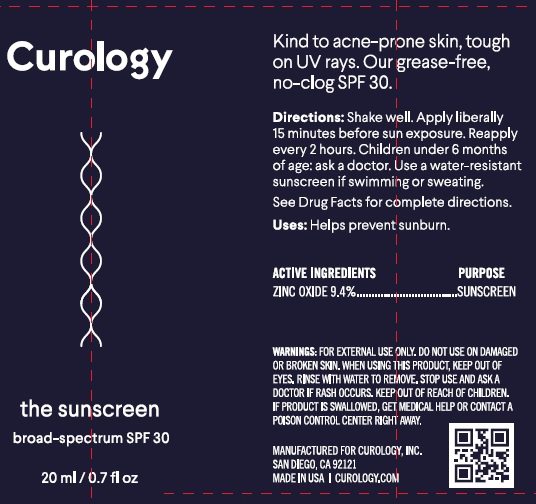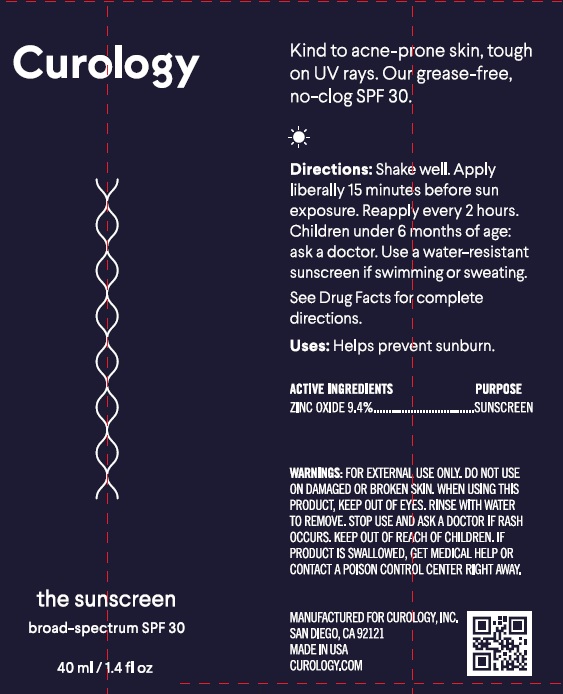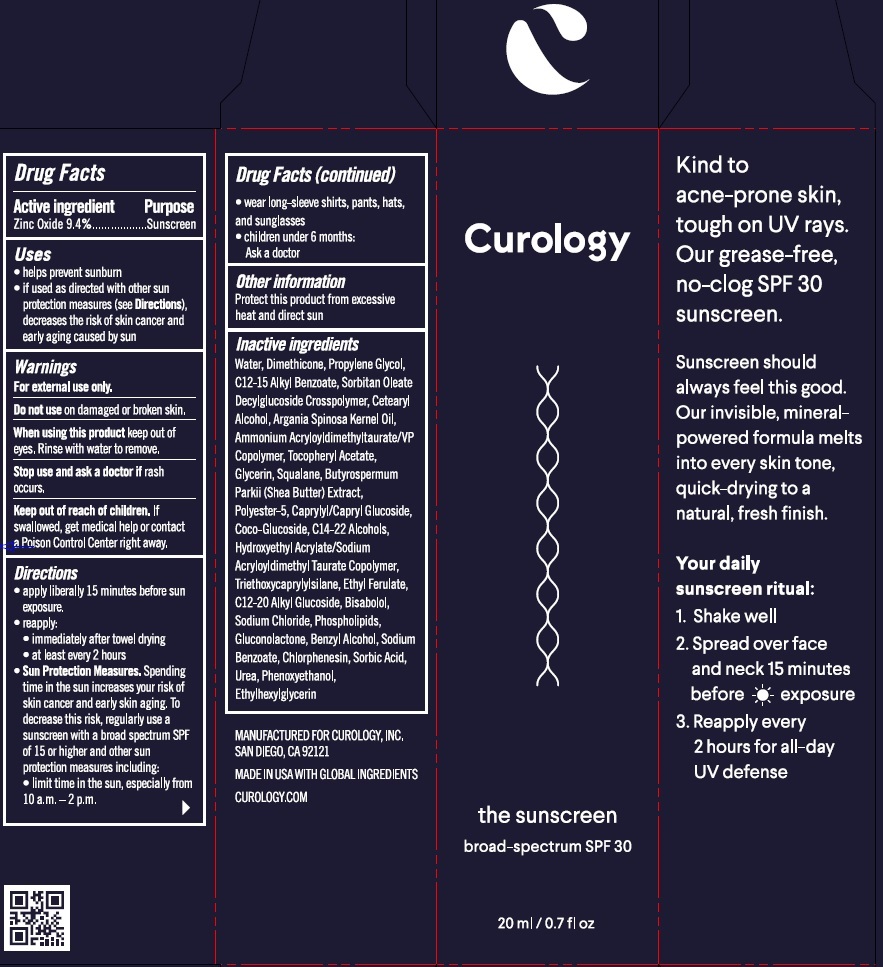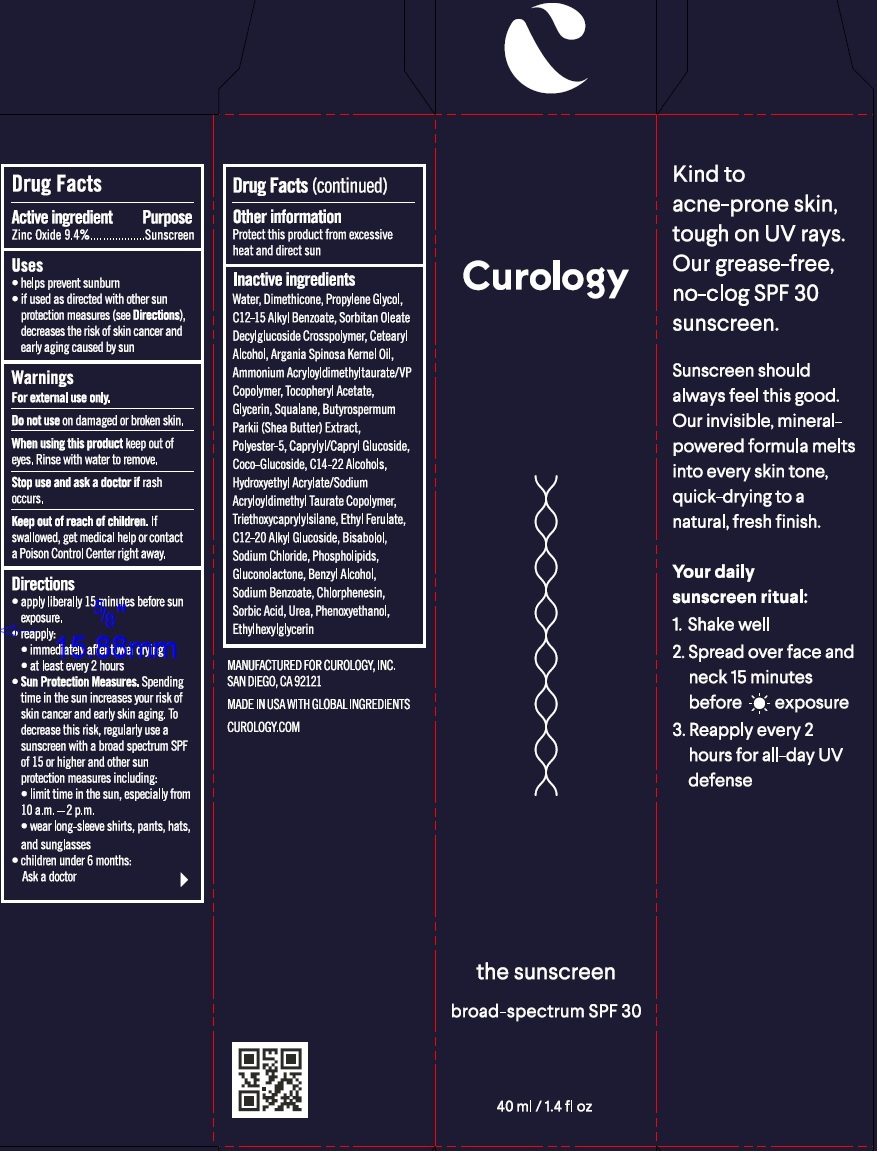 DRUG LABEL: Curology the sunscreen broad spectrum SPF 30
NDC: 82575-032 | Form: CREAM
Manufacturer: Curology Inc.
Category: otc | Type: HUMAN OTC DRUG LABEL
Date: 20231114

ACTIVE INGREDIENTS: ZINC OXIDE 94 mg/1 mL
INACTIVE INGREDIENTS: WATER; DIMETHICONE; PROPYLENE GLYCOL; ALKYL (C12-15) BENZOATE; CETOSTEARYL ALCOHOL; ARGAN OIL; AMMONIUM ACRYLOYLDIMETHYLTAURATE/VP COPOLYMER; .ALPHA.-TOCOPHEROL ACETATE; GLYCERIN; SQUALANE; SHEA BUTTER; CAPRYLYL/CAPRYL OLIGOGLUCOSIDE; COCO GLUCOSIDE; C14-22 ALCOHOLS; TRIETHOXYCAPRYLYLSILANE; ETHYL FERULATE; C12-20 ALKYL GLUCOSIDE; LEVOMENOL; SODIUM CHLORIDE; GLUCONOLACTONE; BENZYL ALCOHOL; SODIUM BENZOATE; CHLORPHENESIN; SORBIC ACID; UREA; PHENOXYETHANOL; ETHYLHEXYLGLYCERIN

Curology the sunscreen broad spectrum SPF 30

Active Ingredient

Zinc Oxide 9.4%

Purpose

Sunscreen

Uses

- helps prevent sunburn
- if used as directed with other sun protection measures (see), decreases the risk of skin cancer and early aging caused by sun Directions

Warnings

For external use only

Do not use

on damaged or broken skin

When using this product

keep out of eyes. Rinse with water to remove.

Stop use and ask a doctor

if rash occurs

Keep out of reach of children.

If swallowed, get medical help or contact a Poison Control Center right away.

Directions

- apply liberally 15 minutes before sun exposure.
- reapply:
- immediately after towel drying
- at least every 2 hours
- Spending time in the sun increases your risk of skin cancer and early skin aging. To decrease this risk, regularly use a sunscreen with a broad spectrum SPF of 15 or higher and other sun protection measures including: Sun Protection Measures.
- limit time in the sun, especially from 10 a.m.-2 p.m.
- wear long-sleeved shirts, pants, hats, and sunglasses
- children under 6 months: Ask a doctor

Other information

Protect this product from excessive heat and direct sun

Inactive Ingredients

Water, Dimethicone, Propylene Glycol, C12-15 Alkyl Benzoate, Sorbitan Oleate Decylglucoside Crosspolymer, Cetearyl Alcohol, Argania Spinosa Kernel Oil, Ammonium Acryloyldimethyltaurate/VP Copolymer, Tocopheryl Acetate, Glycerin, Squalane, Butyrospermum Parkii (Shea Butter) Extract, Polyster-5, Caprylyl/Capryl Glucoside, Coco-Glucosdie, C14-22 Alcohols, Hydroxyethyl Acrylate/Sodium Acryloyldimethyl Taurate Copolymer, Triethoxycaprylylsilane, Ethyl Ferulate, C12-20 Alkyl Glucoside, Bisabolol, Sodium Chloride, Phospholipids, Gluconolactone, Benzyl Alcohol, Sodium Benzoate, Chlorophensin, Sorbic Acid, Urea, Phenoxyethanol, Ethylhexylglycerin